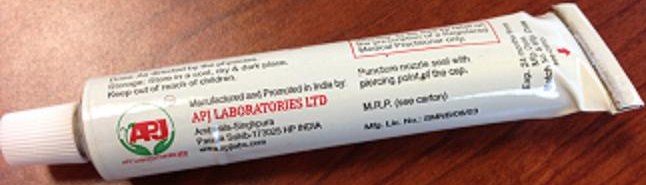 DRUG LABEL: APTRIMAZOLE
NDC: 46084-081 | Form: CREAM
Manufacturer: A P J Laboratories Limited
Category: otc | Type: HUMAN OTC DRUG LABEL
Date: 20130427

ACTIVE INGREDIENTS: CLOTRIMAZOLE 1 g/100 g
INACTIVE INGREDIENTS: PETROLATUM; LIGHT MINERAL OIL; CETOSTEARYL ALCOHOL; EDETIC ACID; CHLOROCRESOL; SODIUM PHOSPHATE, DIBASIC, ANHYDROUS; POLYSORBATE 60; CETETH-20

ACTIVE INGREDIENT

CLOTRIMAZOLE

PURPOSE

Antifungal

Keep out of reach of children. If swallowed, get medical help or contact a Poison Control Center right away.

INDICATIONS AND USAGE

Cures most athlete's foot, jock itch, and ringworm.

Relieves itching, burning, cracking, scaling and discomfort which accompany these conditions.

Do not use on children under 2 years of age unless directed by a doctor.

Avoid contact with eyes.

For athletes foot and ringworm - if irritation occurs, or if there is no improvement within 4 weeks, discontinue use and consult a doctor.

For jock itch - if irritation occurs, or if there is no improvement within two weeks, discontinue use and consult a doctor.

Keep out of reach of children. If swallowed, get medical help or contact a Poison Control Center right away.

Direction:

Clean the affected area and dry thoroughly. Apply a layer of cream over affected area twice daily (morning and night) or as directed by a doctor.

Supervise children in the use of this product.

For athlete's foot, pay special attention to spaces between toes: wear well fitting, ventilated shoes, and change shoes and socks at least once daily.

Foe athlete's foot and ringworm, use daily for 4 weeks.

For jock itch, use daily for 2 weeks.

If conditions persist longer, consult a doctor.

This product is not effective on scalp or nails.

INACTIVE INGREDIENT

PETROLATUM

LIGHT MINERAL OIL

CETOSTEARYL ALCOHOL

EDETIC ACID

CHLOROCRESOL

SODIUM PHOSPHATE, DIBASIC, ANHYDROUS

POLYSORBATE 60

CETETH-20